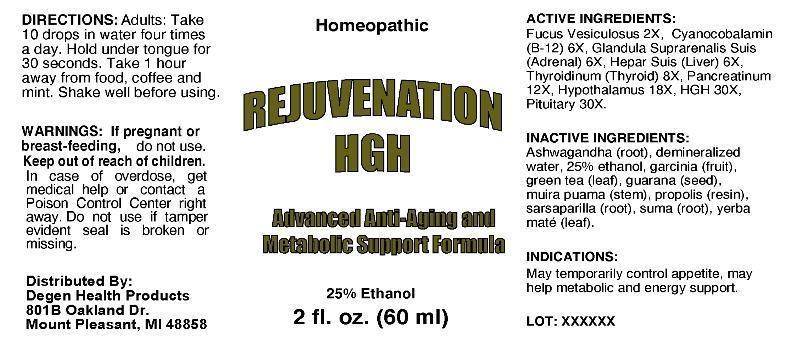 DRUG LABEL: Rejuvenation
NDC: 51812-0001 | Form: LIQUID
Manufacturer: Degen Health Products
Category: homeopathic | Type: HUMAN OTC DRUG LABEL
Date: 20130228

ACTIVE INGREDIENTS: FUCUS VESICULOSUS 2 [hp_X]/1 mL; CYANOCOBALAMIN 6 [hp_X]/1 mL; SUS SCROFA ADRENAL GLAND 6 [hp_X]/1 mL; PORK LIVER 6 [hp_X]/1 mL; SUS SCROFA THYROID 8 [hp_X]/1 mL; PANCRELIPASE 12 [hp_X]/1 mL; SUS SCROFA HYPOTHALAMUS 18 [hp_X]/1 mL; SOMATROPIN 30 [hp_X]/1 mL; SUS SCROFA PITUITARY GLAND 30 [hp_X]/1 mL
INACTIVE INGREDIENTS: GREEN TEA LEAF; WITHANIA SOMNIFERA ROOT; PROPOLIS WAX; PFAFFIA PANICULATA ROOT; PAULLINIA CUPANA SEED; SMILAX REGELII ROOT; PTYCHOPETALUM OLACOIDES WOOD; ILEX PARAGUARIENSIS LEAF; GARCINIA CAMBOGIA FRUIT; WATER; ALCOHOL

Drug Facts

ACTIVE INGREDIENTS

Fucus Vesiculosus 2X, Cyanocobalamin (B-12) 6X, Glandula Suprarenalis Suis (Adrenal) 6X, Hepar Suis (Liver) 6X, Thyroidinum (Thyroid) (Suis) 8X, Pancreatinum 12X, Hypothalamus (Suis) 18X, HGH 30X, Pituitary (Suis) 30X

INDICATIONS

May temporarily control appetite, may help metabolic and energy support.

WARNINGS

If pregnant or breast-feeding, do not use. Keep out of reach of children. In case of overdose, get medical help or contact a Poison Control Center right away. Do not use if tamper evident seal is broken or missing.

DIRECTIONS

Take 10 drops in water four times a day. Hold under tongue for 30 seconds. Take 1 hour away from food, coffee and mint. Shake well before using.

INACTIVE INGREDIENTS

Camellia Sinensis, Somnifera, Propolis, Pfaffia Paniculata, Paullinia Cupana, Smilax Regelii, Ptychopetalum Olacoides, Ilex Paraguariensis, Garcinia Cambogia, Water, Ethanol 25%

KEEP OUT OF REACH OF CHILDREN

In case of overdose, get medical help or contact a Poison Control Center right away.

INDICATIONS AND USAGE

May temporarily control appetite, may help metabolic and energy support.

QUESTIONS

Distributed By:

Degan Health Products

801B Oakland Dr.

Mount Pleasant, MI 48858

PACKAGE LABEL

Homeopathic

REJUVENATION

HGH

Advanced Anti-Aging and

Metabolic Support Formula

2 fl. oz. (60 ml)